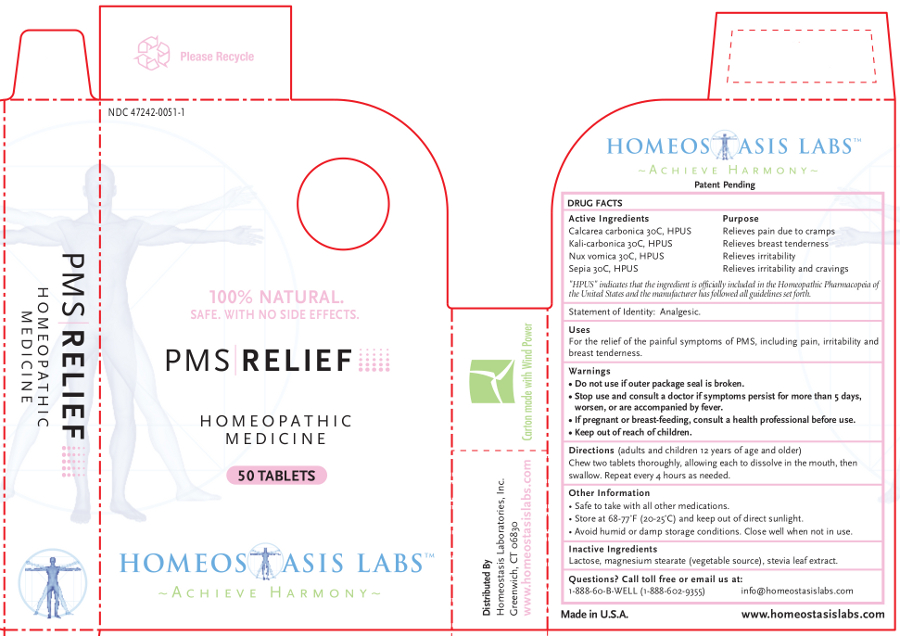 DRUG LABEL: PMS RELIEF
NDC: 47242-0051 | Form: TABLET, CHEWABLE
Manufacturer: Homeostasis Laboratories, Inc.
Category: homeopathic | Type: HUMAN OTC DRUG LABEL
Date: 20121114

ACTIVE INGREDIENTS: OYSTER SHELL CALCIUM CARBONATE, CRUDE 30 [hp_C]/1 1; POTASSIUM CARBONATE 30 [hp_C]/1 1; STRYCHNOS NUX-VOMICA SEED 30 [hp_C]/1 1; SEPIA OFFICINALIS JUICE 30 [hp_C]/1 1
INACTIVE INGREDIENTS: LACTOSE; MAGNESIUM STEARATE; STEVIA REBAUDIUNA LEAF

PMS RELIEF

Active Ingredients | Purpose
Calcarea carbonica 30C, HPUS | Relieves pain due to cramps
Kali-carbonica 30C, HPUS | Relieves breast tenderness
Nux vomica 30C, HPUS | Relieves irritability
Sepia 30C, HPUS | Relieves irritability and cravings

"HPUS" indicates that the ingredient is officially included in the Homeopathic Pharmacopeia of the United States and the manufacturer has followed all guidelines set forth.

Statement of Identity: Analgesic.

Uses

For the relief of the painful symptoms of PMS, including pain, irritability and breast tenderness.

Warnings

- Do not use if outer package seal is broken.
- Stop use and consult a doctor if symptoms persist for more than 5 days, worsen, or are accompanied by fever.

PREGNANCY OR BREAST FEEDING

- If pregnant or breast-feeding, consult a health professional before use.

- Keep out of reach of children.

Directions

(adults and children 12 years of age and older)

Chew two tablets thoroughly, allowing each to dissolve in the mouth, then swallow. Repeat every 4 hours as needed.

Other information

- Safe to take with all other medications.
- Store at 68-77°F (20-25°C) and keep out of direct sunlight.
- Avoid humid or damp storage conditions. Close well when not in use.

Inactive Ingredients

Lactose, magnesium stearate (vegetable source), stevia leaf extract.

Questions? Call toll free or email us at:

1-888-60-B-WELL (1-888-602-9355)

info@homeostasislabs.com